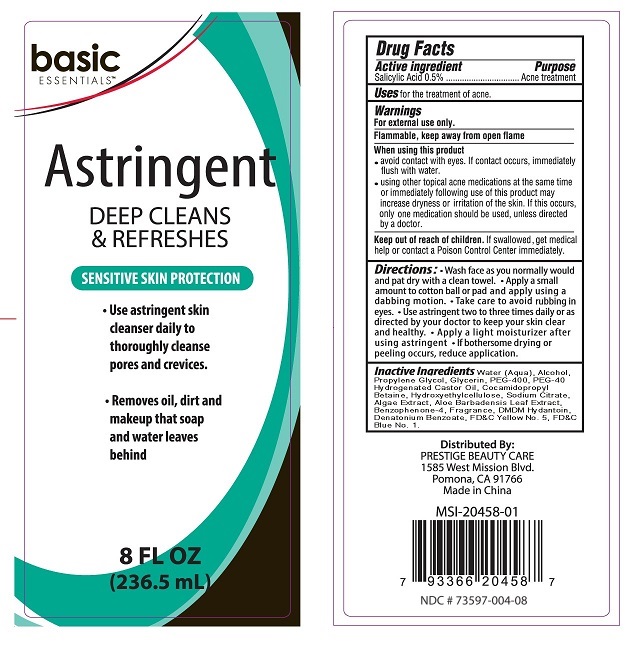 DRUG LABEL: Basic Essentials Astringent
NDC: 73597-004 | Form: LIQUID
Manufacturer: Mission Series Inc. dpa Prestige Beauty Care
Category: otc | Type: HUMAN OTC DRUG LABEL
Date: 20250123

ACTIVE INGREDIENTS: SALICYLIC ACID 0.05 g/100 mL
INACTIVE INGREDIENTS: SODIUM CITRATE; PHYMATOLITHON CALCAREUM; ALOE VERA LEAF; DENATONIUM BENZOATE; FD&C YELLOW NO. 5; FD&C BLUE NO. 1; WATER; POLYOXYL 40 HYDROGENATED CASTOR OIL; PROPYLENE GLYCOL; POLYETHYLENE GLYCOL 400; COCAMIDOPROPYL BETAINE; HYDROXYETHYL CELLULOSE, UNSPECIFIED; SULISOBENZONE; GLYCERIN; DMDM HYDANTOIN; ALCOHOL

Basic Essentials Astringent

Active Ingredient

Active Ingredients

Salicylic Acid 0.5%

Purpose

Acne Treatment

Indications & Usage

Uses: for the treatment of acne.

Warnings

For external use only.

Flammable, keep away from open flame.

When using this product

• avoid contact with the eyes. If contact occurs, immediately flush thoroughly with water.

Ask a doctor

• using other topical acne medications at the same time or immediately following use of this product may increase dryness or irritation of the skin. If this occurs, only one medication should be used, unless directed by a doctor.

Keep out of reach of children. If swallowed, get medical help or contact a Poison Control Center immediately.

Directions

Directions: • Wash face as you normally would and pat dry with a clean towel. • Apply a small amount to cotton ball or pad and apply using a dabbing motion. • Take care to avoid rubbing in eyes. • Use astringent two to three times daily or as directed by your doctor to keep your skin clear and healthy. • Apply a light moisturizer after using astringent. • If bothersome drying or peeling occurs, reduce application.

Inactive Ingredients

Inactive ingredients Water (Aqua), Alcohol, Propylene Glycol, Glycerin, PEG-400, PEG-40 Hydrogenated Castor Oil, Cocamidopropyl Betaine, Hydroxyethylcellulose, Sodium Citrate, Algae Extract, Aloe Barbadensis Leaf Extract, Benzophenone-4, Fragrance, DMDM Hydantoin, Denatonium Benzoate, FD&C Yellow No. 5, FD&C Blue No. 1.

Distributed by

PRESTIGE BEAUTY CARE

1585 West Mission Blvd.

Pomona, CA 91766

Made in China